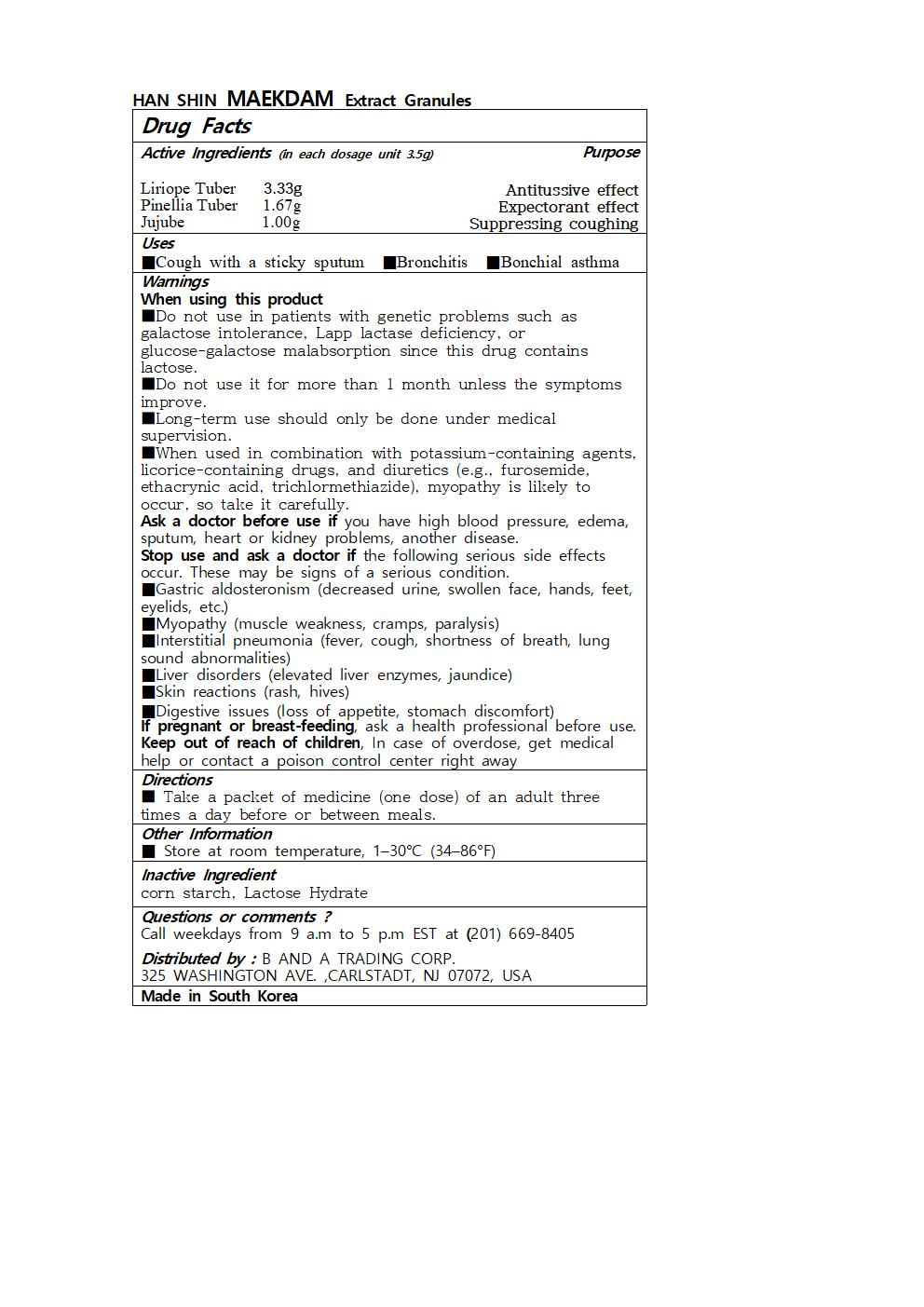 DRUG LABEL: HAN SHIN MAEKDAM Extract Granules
NDC: 73466-0032 | Form: GRANULE
Manufacturer: MISOCOS
Category: otc | Type: HUMAN OTC DRUG LABEL
Date: 20250301

ACTIVE INGREDIENTS: LIRIOPE SPICATA TUBER 3.33 g/3.5 g
INACTIVE INGREDIENTS: ZIZIPHUS JUJUBA WHOLE; LACTOSE MONOHYDRATE; PINELLIA TERNATA ROOT

Drug Facts

ACTIVE INGREDIENT

Liriope Tuber 3.33g

PinelliaTuber 1.67g

Jujube 1.00g

INACTIVE INGREDIENT

corn starch, Lactose Hydrate

PURPOSE

■Cough with a sticky sputum ■Bronchitis ■Bonchial asthma

keep out of reach of the children

INDICATIONS AND USAGE

■ Take a packet of medicine (one dose) of an adult three times a day before or between meals.

Warnings

When using this product

■Do not use in patients with genetic problems such as galactose intolerance, Lapp lactase deficiency, or glucose-galactose malabsorption since this drug contains lactose.

■Do not use it for more than 1 month unless the symptoms improve.

■Long-term use should only be done under medical supervision.

■When used in combination with potassium-containing agents, licorice-containing drugs, and diuretics (e.g., furosemide, ethacrynic acid, trichlormethiazide), myopathy is likely to occur, so take it carefully.

Ask a doctor before use if you have high blood pressure, edema, sputum, heart or kidney problems, another disease.

Stop use and ask a doctor if the following serious side effects occur. These may be signs of a serious condition.

■Gastric aldosteronism (decreased urine, swollen face, hands, feet, eyelids, etc.)

■Myopathy (muscle weakness, cramps, paralysis)

■Interstitial pneumonia (fever, cough, shortness of breath, lung sound abnormalities)

■Liver disorders (elevated liver enzymes, jaundice)

■Skin reactions (rash, hives)

■Digestive issues (loss of appetite, stomach discomfort)

If pregnant or breast-feeding, ask a health professional before use.

Keep out of reach of children, In case of overdose, get medical help or contact a poison control center right away

DOSAGE AND ADMINISTRATION

for oral use only